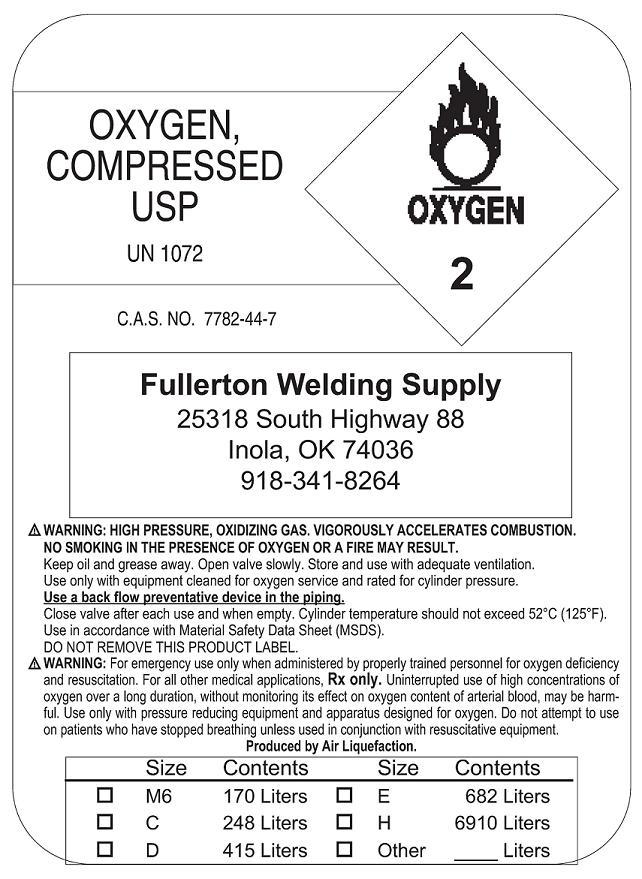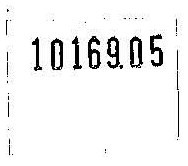 DRUG LABEL: Oxygen
NDC: 42751-1072 | Form: GAS
Manufacturer: Fullerton Welding Supply
Category: prescription | Type: HUMAN PRESCRIPTION DRUG LABEL
Date: 20091112

ACTIVE INGREDIENTS: Oxygen 99 L/100 L

Oxygen